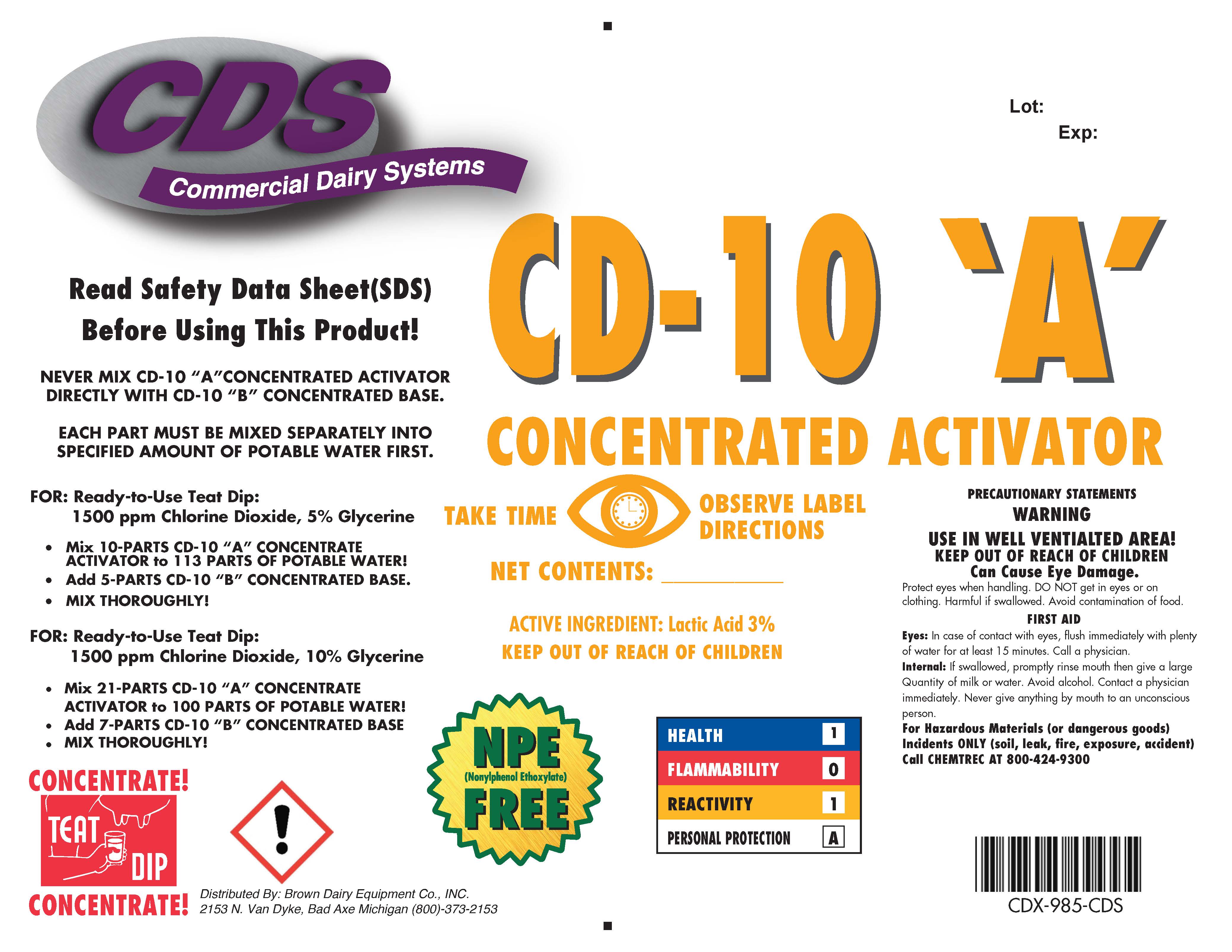 DRUG LABEL: CD-10 A Concentrated Activator
NDC: 62897-985 | Form: CONCENTRATE
Manufacturer: Brown Dairy Equipment Co., Inc
Category: animal | Type: OTC ANIMAL DRUG LABEL
Date: 20190412

ACTIVE INGREDIENTS: LACTIC ACID 3 g/1 L
INACTIVE INGREDIENTS: METHYLPARABEN; GLYCERIN; ANHYDROUS CITRIC ACID; C12-15 ALCOHOLS; WATER; FD&C BLUE NO. 1

CD-10 'A'
CONCENTRATED ACTIVATOR

WARNINGS AND PRECAUTIONS

CD-10 'A'

CONCENTRATED ACTIVATOR

TAKE TIME OBSERVE LABEL DIRECTIONS

NET CONTENTS:

ACTIVE INGREDIENT: Lactic Acid 3%

KEEP OUT OF REACH OF CHILDREN

WARNINGS

HEALTH 1

FLAMMABILITY 0

REACTIVITY 1

PERSONAL PROTECTION A

NPE

(Nonylphenol Ethoxylate)

FEEE

WARNINGS AND PRECAUTIONS

Read Safety Data Sheet (SDS) Before Using This Product!

NEVER MIX CD-10 "A" CONCENTRATED ACTIATOR DIRECTLY WITH CD-10 "B" CONCENTRATED BASE.

EACH PART MUST BE MIXED SPEARATELY IN SPECIFIED AMOUNT OF POTABLE WATER FIRST.

FOR: Ready-to-Use Teat Dip:

1500 ppm Chlorine Dioxide, 5% Glycerine

- Mix 10-PARTS CD-10 "A" CONCENTRATE ACTIVATOR to 113 PARTS OF POTABLE WATER!
- Add 5-PARTS CD-10 "B" CONCENTRATED BASE.
- MIX THOROUGHLY!

FOR: Ready-to-Use Teat Dip:

1500 ppm Chlorine Dioxide, 10% Glycerine

- Mix 21-PARTS CD-10 "A" CONCENTRATE ACTIVATOR to 100 PARTS OF POTABLE WATER!
- Add 7-PARTS CD-10 "B" CONCENTRATED BASE
- MIX THOROUGHLY!

WARNINGS

CONCENTRATE!

TEAT DIP

CONCENTRATE!

PRECAUTIONS

PRECAUTIONARY STATEMENTS

WARNING

USE IN WELL VENTILATED AREA!

KEEP OUT OF REACH OF CHILDREN

Can Cause Eye Damage.

Protect eyes when handling. DO NOT get in eyes or on clothing. Harmful if swallowed. Avoid contamination of food.

FIRST AID

Eyes: In case of contact with eyes, flush immediately with plenty of water for at least 15 minutes. Call a physician.

Internal: If swallowed, promptly rinse mouth then give a large Quantity of milk or water. Avoid alcohol. Contact a physician immediately. Never give anything by mouth to an unconscious person.

For Hazardous Materials (or dangerous goods) Incidents ONLY (soil, leak, fire, exposure, accident)

Call CHEMTREC AT 800-424-9300